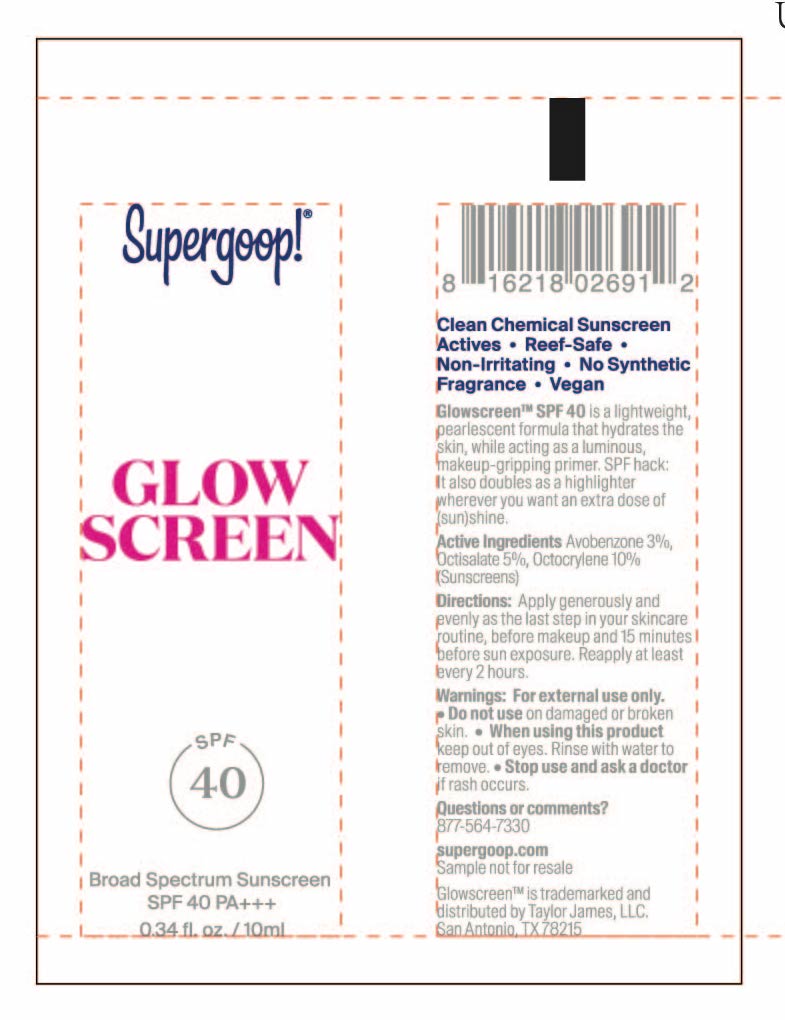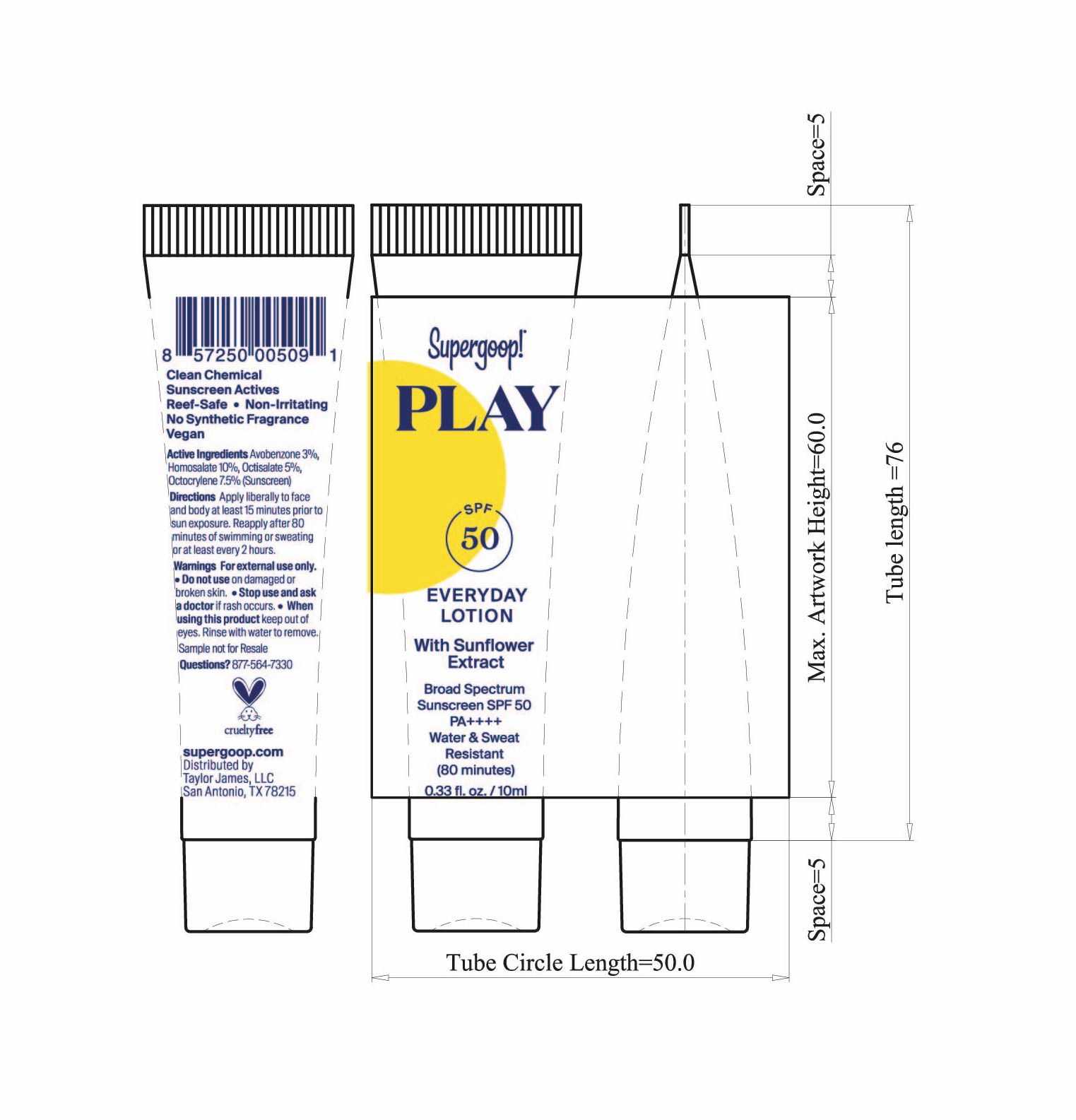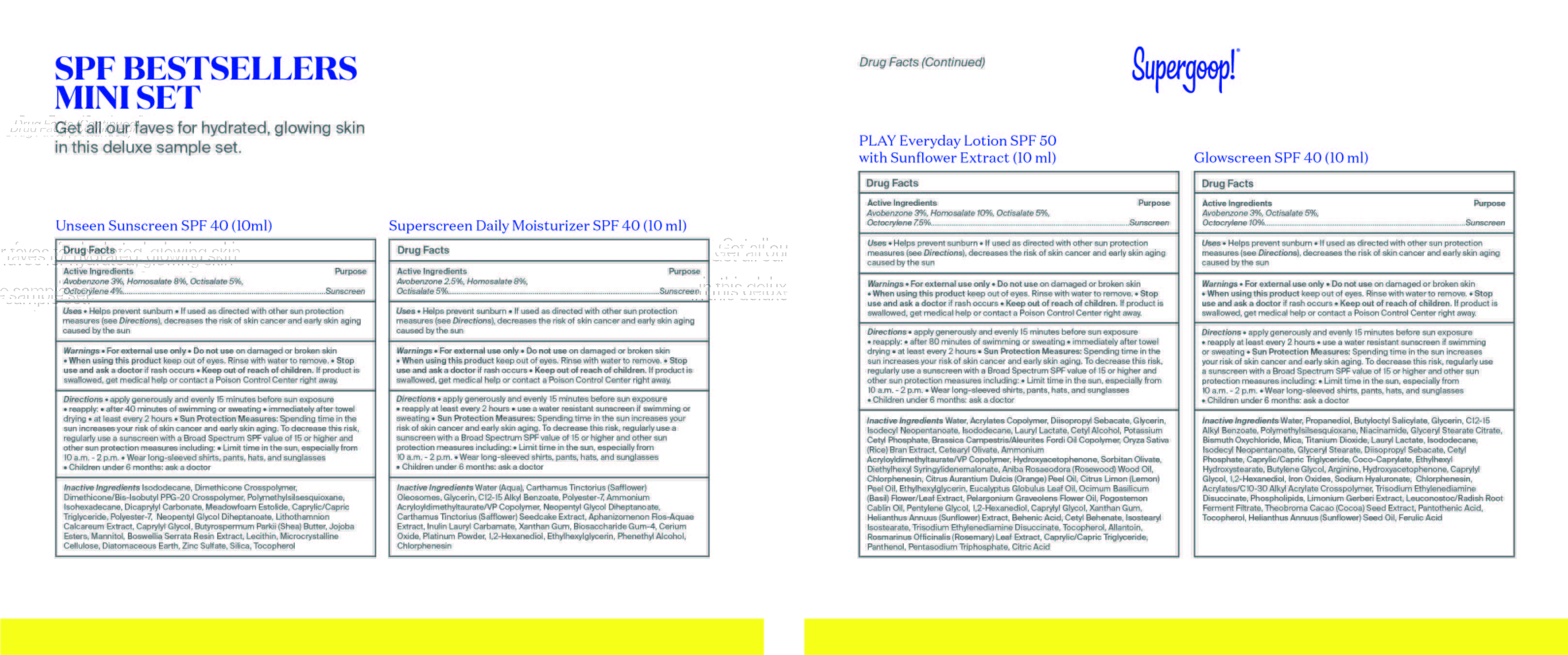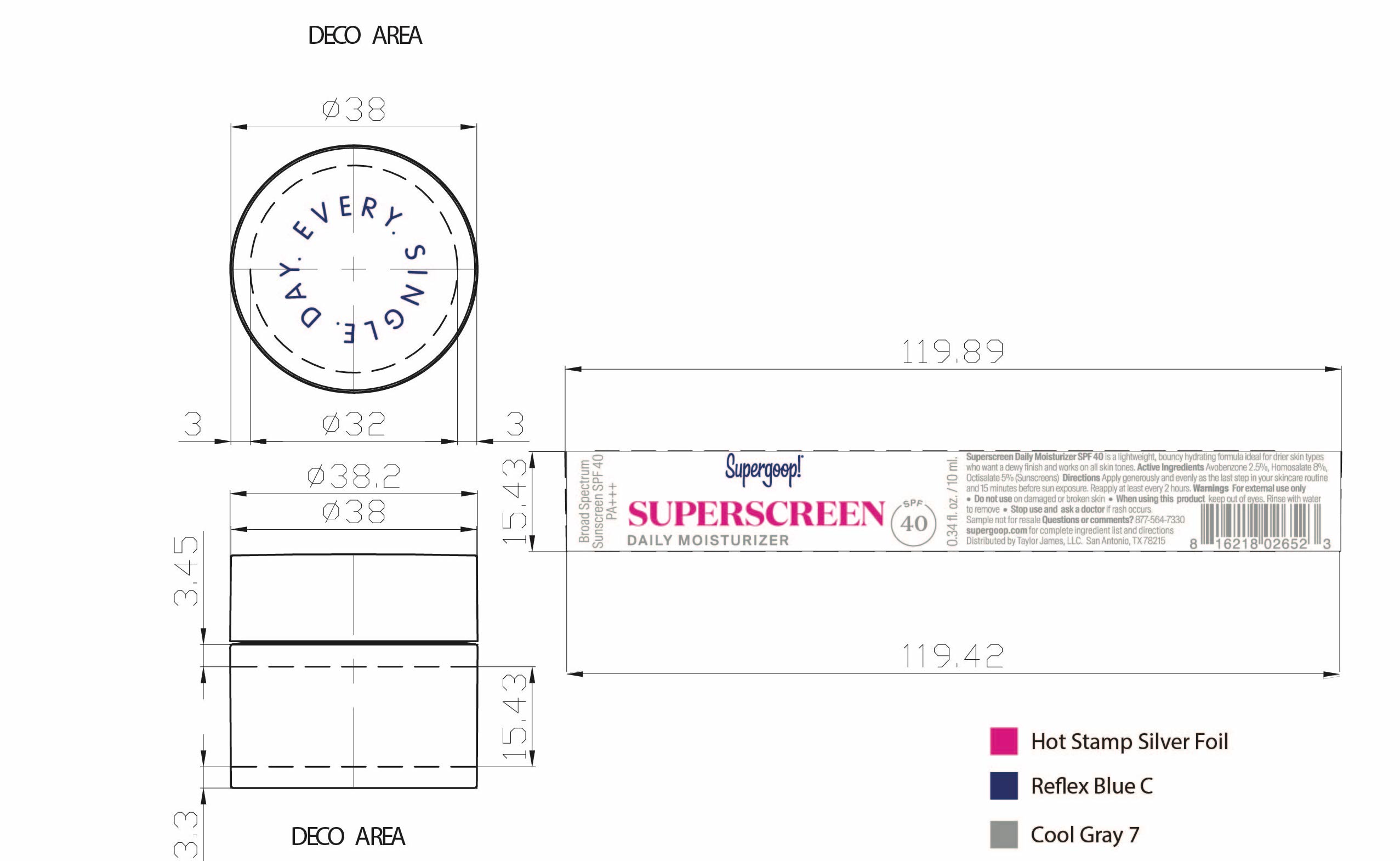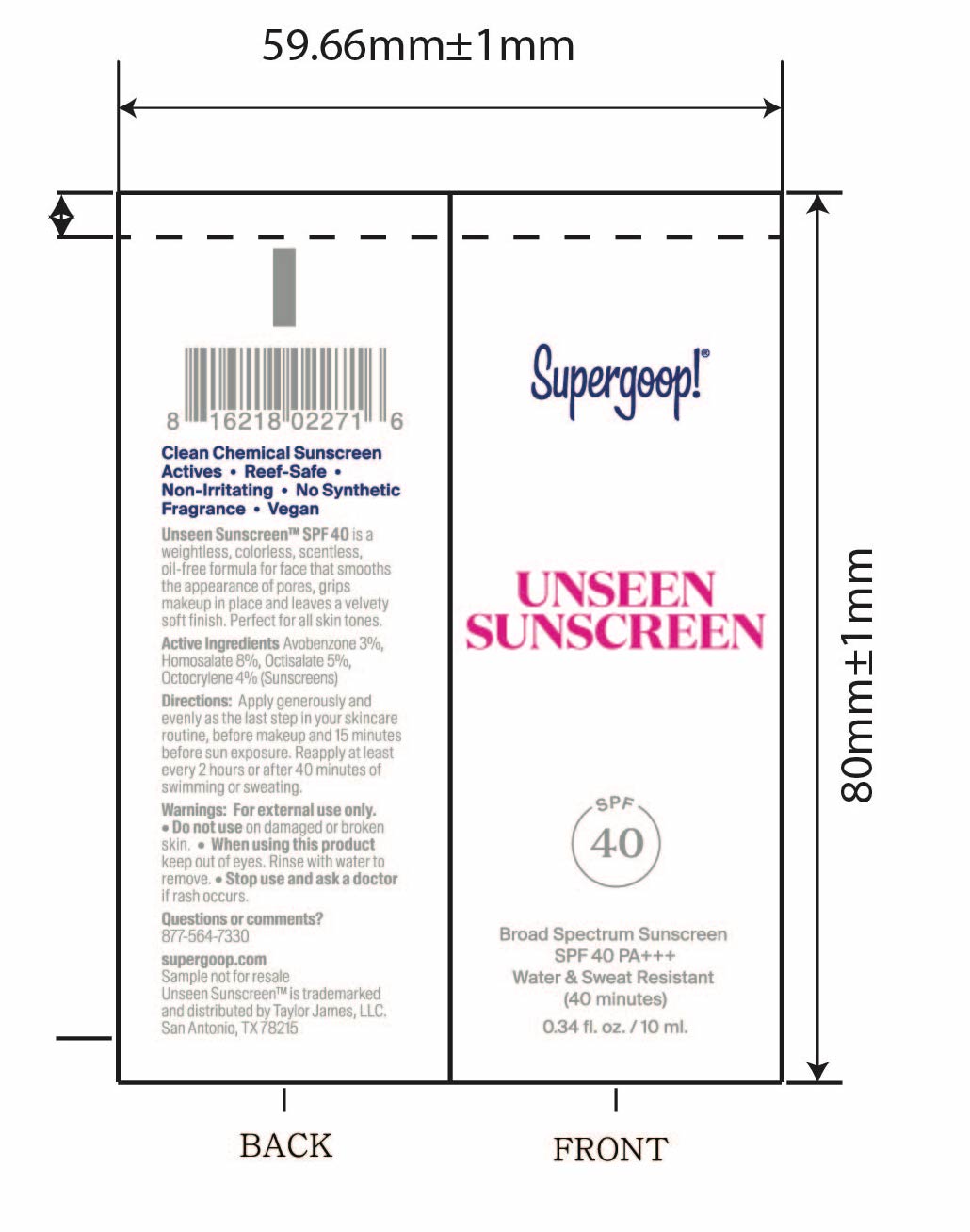 DRUG LABEL: SPF Best Sellers Mini Kit
NDC: 82384-0010 | Form: KIT | Route: TOPICAL
Manufacturer: System Beauty, LLC
Category: otc | Type: HUMAN OTC DRUG LABEL
Date: 20211207

ACTIVE INGREDIENTS: OCTISALATE 5 g/100 mL; AVOBENZONE 3 g/100 mL; HOMOSALATE 8 g/100 mL; OCTOCRYLENE 4 g/100 mL; AVOBENZONE 3 g/100 mL; OCTISALATE 5 g/100 mL; OCTOCRYLENE 10 g/100 mL; HOMOSALATE 10 g/100 mL; OCTISALATE 5 g/100 mL; AVOBENZONE 3 g/100 mL; OCTOCRYLENE 7.5 g/100 mL; HOMOSALATE 8 g/100 mL; OCTISALATE 5 g/100 mL; AVOBENZONE 2.5 g/100 mL
INACTIVE INGREDIENTS: DICAPRYLYL CARBONATE; MICROCRYSTALLINE CELLULOSE; POLYMETHYLSILSESQUIOXANE (4.5 MICRONS); SILICON DIOXIDE; PHYMATOLITHON CALCAREUM; CAPRYLYL GLYCOL; SHEA BUTTER; MANNITOL; TOCOPHEROL; ISODODECANE; DIATOMACEOUS EARTH; ZINC SULFATE; DIMETHICONE CROSSPOLYMER (450000 MPA.S AT 12% IN CYCLOPENTASILOXANE); LECITHIN, SOYBEAN; INDIAN FRANKINCENSE; POLYESTER-7; MEDIUM-CHAIN TRIGLYCERIDES; NEOPENTYL GLYCOL DIHEPTANOATE; DIMETHICONE/BIS-ISOBUTYL PPG-20 CROSSPOLYMER; ISOHEXADECANE; FERROSOFERRIC OXIDE; PANTOTHENIC ACID; SUNFLOWER OIL; GLYCERIN; TOCOPHEROL; FERULIC ACID; CHLORPHENESIN; CARBOMER COPOLYMER TYPE A (ALLYL PENTAERYTHRITOL CROSSLINKED); OMEGA-3 FATTY ACIDS; LEUCONOSTOC/RADISH ROOT FERMENT FILTRATE; COCOA; MEDIUM-CHAIN TRIGLYCERIDES; ETHYLHEXYL HYDROXYSTEARATE; FERRIC OXIDE RED; FERRIC OXIDE YELLOW; PROPANEDIOL; BUTYLOCTYL SALICYLATE; ALKYL (C12-15) BENZOATE; NIACINAMIDE; BUTYLENE GLYCOL; ARGININE; HYDROXYACETOPHENONE; CAPRYLYL GLYCOL; 1,2-HEXANEDIOL; TRISODIUM ETHYLENEDIAMINE DISUCCINATE; WATER; POLYMETHYLSILSESQUIOXANE (4.5 MICRONS); GLYCERYL STEARATE CITRATE; BISMUTH OXYCHLORIDE; MICA; TITANIUM DIOXIDE; LAURYL LACTATE; ISODODECANE; ISODECYL NEOPENTANOATE; GLYCERYL MONOSTEARATE; DIISOPROPYL SEBACATE; CETYL PHOSPHATE; COCO-CAPRYLATE; HYALURONATE SODIUM; TRISODIUM ETHYLENEDIAMINE DISUCCINATE; LAURYL LACTATE; ORANGE OIL, COLD PRESSED; OCIMUM BASILICUM FLOWERING TOP; ETHYLHEXYLGLYCERIN; CITRIC ACID MONOHYDRATE; PELARGONIUM GRAVEOLENS FLOWER OIL; POGOSTEMON CABLIN LEAF OIL; PENTYLENE GLYCOL; ALLANTOIN; BEHENIC ACID; LEMON OIL, COLD PRESSED; EUCALYPTUS OIL; HELIANTHUS ANNUUS FLOWERING TOP; CETYL BEHENATE; RICE BRAN; CETEARYL OLIVATE; ROSEWOOD OIL; CHLORPHENESIN; ROSEMARY; MEDIUM-CHAIN TRIGLYCERIDES; SODIUM TRIPOLYPHOSPHATE ANHYDROUS; BUTYL ACRYLATE/METHYL METHACRYLATE/METHACRYLIC ACID COPOLYMER (18000 MW); DIISOPROPYL SEBACATE; 1,2-HEXANEDIOL; CAPRYLYL GLYCOL; XANTHAN GUM; ISOSTEARYL ISOSTEARATE; TOCOPHEROL; CETYL ALCOHOL; POTASSIUM CETYL PHOSPHATE; AMMONIUM ACRYLOYLDIMETHYLTAURATE/VP COPOLYMER; HYDROXYACETOPHENONE; DIETHYLHEXYL SYRINGYLIDENEMALONATE; ISODECYL NEOPENTANOATE; ISODODECANE; SORBITAN OLIVATE; PANTHENOL; WATER; GLYCERIN; CARTHAMUS TINCTORIUS SEED OLEOSOMES; XANTHAN GUM; PLATINUM; 1,2-HEXANEDIOL; ETHYLHEXYLGLYCERIN; CERIC OXIDE; WATER; GLYCERIN; ALKYL (C12-15) BENZOATE; POLYESTER-7; AMMONIUM ACRYLOYLDIMETHYLTAURATE/VP COPOLYMER; NEOPENTYL GLYCOL DIHEPTANOATE; CARTHAMUS TINCTORIUS SEEDCAKE; APHANIZOMENON FLOSAQUAE; BIOSACCHARIDE GUM-4; PHENYLETHYL ALCOHOL; CHLORPHENESIN

SPF Best Sellers Mini Kit

Play Everyday Sunscreen SPF 50 with Sunflower extract Active ingredients

Active Ingredients Purpose

Avobenzone 3% Sunscreen

Homosalate 10% Sunscreen

Octisalate 5% Sunscreen

Octocrylene 7.5% Sunscreen

Unseen Sunscreen SPF 40 active ingredients

Active Ingredients Purpose

Avobenzone 3% Sunscreen

Homosalate 8% Sunscreen

Octocrylene 4% Sunscreen

Octisalate 5% Sunscreen

Superscreen Daily Moisturizer SPF 40

Active Ingredients Purpose

Avobenzone 2.5% Sunscreen

Homosalate 8% Sunscreen

Octisalate 5% Sunscreen

Glow Screen SPF 40

Active Ingredients Purpose

Avobenzone 3% Sunscreen

Octisalate 5% Sunscreen

Octocrylene10% Sunscreen

Uses

Helps Prevent Sunburn

If used as directed with other sun protection measures (see Directions), decreases the risk of Skin cancer and early skin aging caused by the sun

Keep out of reach of children. If swallowed, get medical help or contact a Poison Control Center right away

Stop use and ask a doctor if rash occurs

Warnings

For External use only

Do not use on damaged or broken skin

When using this product, Keep out of eyes. Rinse with water to remove

Play Everyday Lotion SPF 50 with Sunflower Extract Directions

Directions

- Apply generously and evenly 15 minutes before sun exposure
- Reapply:after 80 minutes of swimming or sweating

immediately after towel drying
at least every 2 hours

- Sun Protection Measures. Spending time in the sun increases your risk of skin

cancer and early skin aging. To decrease this risk, regularly use a sunscreen
with broad spectrum SPF of 15 or higher and other sun protection measures
including:

- limit time in the sun, especially from 10 a.m. - 2 p.m.
- Wear Long-sleeved shirts, pants, hats, and sunglasses
- Children under 6 months: Ask a doctor

Directions

- Apply generously and evenly 15 minutes before sun exposure
- Reapply:after 40 minutes of swimming or sweating

immediately after towel drying
at least every 2 hours

- Sun Protection Measures. Spending time in the sun increases your risk of skin

cancer and early skin aging. To decrease this risk, regularly use a sunscreen
with broad spectrum SPF of 15 or higher and other sun protection measures
including:

- limit time in the sun, especially from 10 a.m. - 2 p.m.
- Wear Long-sleeved shirts, pants, hats, and sunglasses
- Children under 6 months: Ask a doctor

Unseen Sunscreen SPF 40 Inactive Ingredients

Inactive Ingredients

Isododecane, Dimethicone Crosspolymer, Dimethicone/Bis-Isobutyl PPG-20 Crosspolymer, Polymethylsilsesquioxane, Isohexadecane, Dicrapylyl Carbonate, Meadowfoam Estolide, Caprylic/Capric Triglyceride, Polyester-7, Neopentyl Glycol Diheptanoate, Lithothamnion Calcareum Extract,Butyrospermum Parkii (Shea) Butter, Jojoba Esters, Mannitol, Boswellia Serrata Resin Extract, Lecithin, Microcrystalline Cellulose, Diatomaceous Earth, Zinc Sulfate, Silica, Tocopherol

Sunscreen Daily Moisturizer SPF 40 Inactive Ingredients

Inactive ingredients Water, Cartamus Tinctorius (safflower) Olesomes, Glycerin, C12-15 Alkyl Benzoate, Polyester-7, Ammonium Acryloyldimethyldimethyltaurate/VP Copolymer, Neopentyl Glycol Diheptanoate, Carthamus Tinctorius (Safflower) Seedcake extract, Aphanizomenon Flos-Aquae Extract, Inulin Lauryl Carbamate, Xanthan Gum, Biosaccharide Gum-4, Cerium Oxide, Platinum Powder, 1,2-hexanediol, Ethylhexylglycerin, Phenethyl Alcohol, Chlorphenesin

Play Everyday Sunscreen SPF 50 with sunflower Inactive ingredients

Inactive ingredients

Water, Acrylates Copolymer, Diisopropyl Sebacate, Glycerin, Isodecyl Neopentanoate, Isododecane, Lauryl Lactate, Cetyl Alcohol, Potassium Cetyl Phosphate, Brassica Camprestris/Aleurites Fordi Copolymer, Oryza Sativa (Rice) Bran Extract, Cetearyl Olivate, Ammonium Acryloyldimethyltaurate/VP Copolymer, Hydroxyacetophenone, Sorbitan Olivate, Diethylhexyl Syringylidenemalonate, Aniba Rosaeodora (Rosewood) Wood Oil, Chlorphenesin, Citrus Aurantium Dulcis (Orange) Peel Oil, Citrus Limon (Lemon) Peel Oil, Ethylhexylglycerin, Eucalyptus Globulus Leaf Oil, Ocimum Bascilicum (Basil) Flower/Leaf Extract, Pelargonium Graveolens Flower Oil, Pogostemon Cablin Oil, Pentylene Glycol, 1,2-hexanediol, Caprylyl Glycol, Xanthan Gum, Helianthus Annuus (Sunflower) Extract, Behenic Acid, Cetyl Behenate, Isostearyl Isostearate, Trisodium Ethylenediamene Disuccinate, Tocopherol, Allantoin, Rosmarinus Officinalis (Rosemary) Leaf Extract, Caprylic/Capric Triglyceride,Panthenol, Pentasodium Triphosphate, Citric Acid

Glowscreen SPF 40 Inactive ingredients

Inactive Ingredients

Water, Propanediol, Butyloctyl Salicylate, Glycerin, C12-15 Alkyl Benzoate, Polymethylsilsesquioxane, Niacinamide, Glyceryl Stearate Citrate, Bismuth Oxychloride, Mica, Titanium Dioxide, Lauryl Lactate, Isododecane, Isodecyl Neopentanoate, Glyceryl Stearate Citrate, Bismuth Oxychloride, Mica, Titanium Dioxide, Lauryl Lactate, Isododecane, Isodecyl Neopentanoate, Glyceryl Stearate, Diisopropyl Sebacate, Cetyl Phosphate, Caprylic/Capric Triglyceride, Coco-Caprylate, Ethylhexyl Hydroxystearate, Butylene Glycol, Arginine, Hydroxyacetophenone, Caprylyl Glycol, 1,2-Hexanediol, Iron Oxides, Sodium Hyaluronate, Chlorphenesin, Acrylates/C10-30 Alkyl Acrylate Crosspolymer, Trisodium Ethylenediamine Disuccinate, Phospholipids, Limonium Gerberi Extract, Leuconostoc/Radish Root Ferment Filtrate, Theobroma Cocoa (Cocoa) Seed Extract, Pantothenic Acid , Tocopherol, Helianthus Annuus (Sunflower) Seed Oil, Ferulic Acid

Bestseller Kit

SPF Bestsellers Mini Set

Get all our faves for hydrated, glowing skin in this deluxe sample set

Unseen Sunscreen SPF 40 (10ml)

Superscreen Daily Moisturizer SPF 40 (10ml)

PLAY Everyday LotionSPF 50 with Sunflower Extract (10ml)

Glowscreen SPF 40 (10ml)

Unseen Sunscreen tube

Unseen Sunscreen SPF 40

Broad Spectrum Sunscreen

SPF 40 PA+++

Water & Sweat Resistant (40 Minutes)

0.34 fl. oz./ 10 ml

Superscreen Daily Moisturizer SPF 40

Superscreen Daily Moisturizer

Broad Spectrum Sunscreen SPF 40 PA +++

0.34 fl. oz./ 10 ml.

PLAY Everyday Lotion SPF 50 Sunflower extract tube

PLAY

Everyday Lotion

with Sunflower Extract

Broad Spectrum Sunscreen SPF 50

PA ++++

Water & Sweat Resistant (80 minutes)

0.33 fl oz./ 10ml

Glowscreen SPF 40 tube

Glowscreen

Broad Spectrum SPF 40 PA +++

0.34 fl. oz. / 10 ml